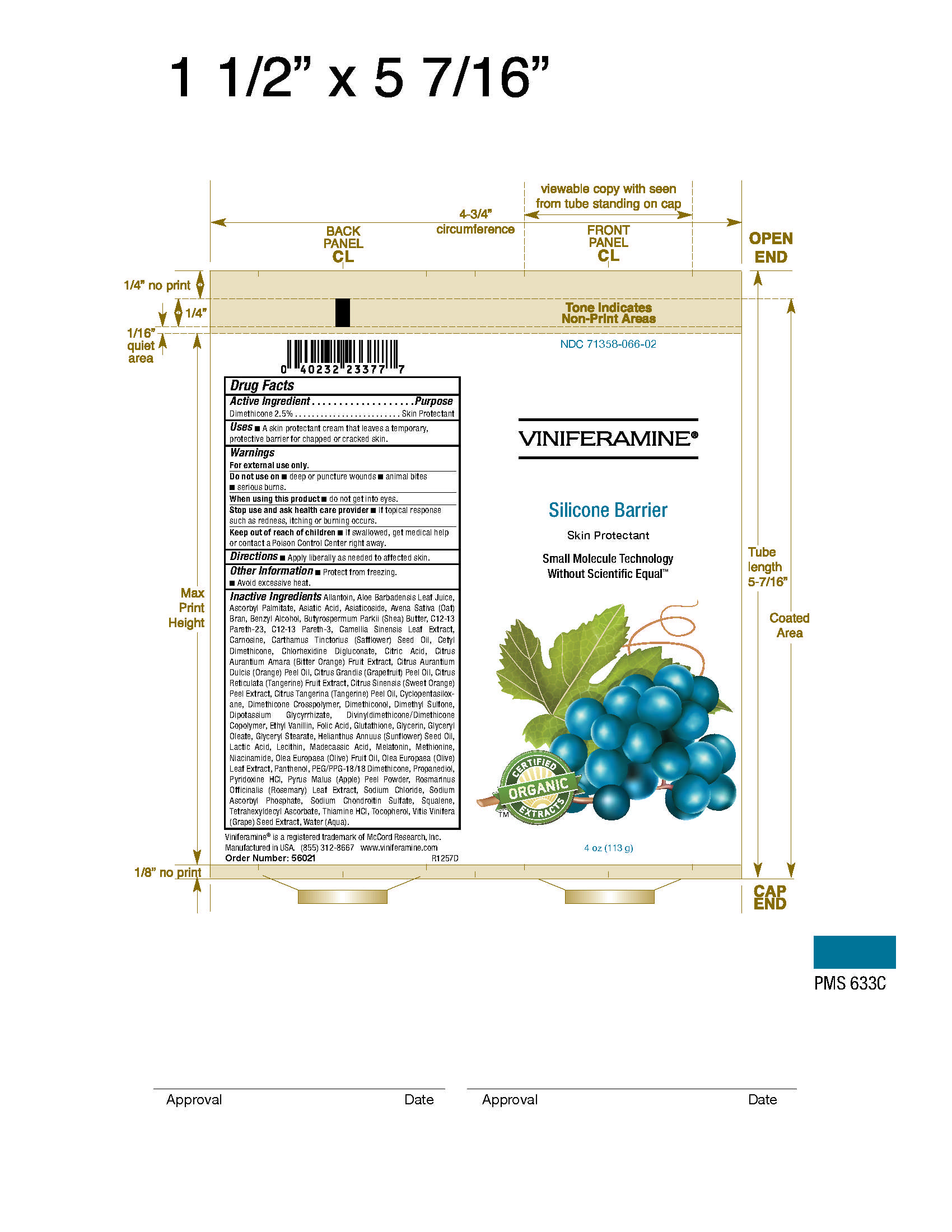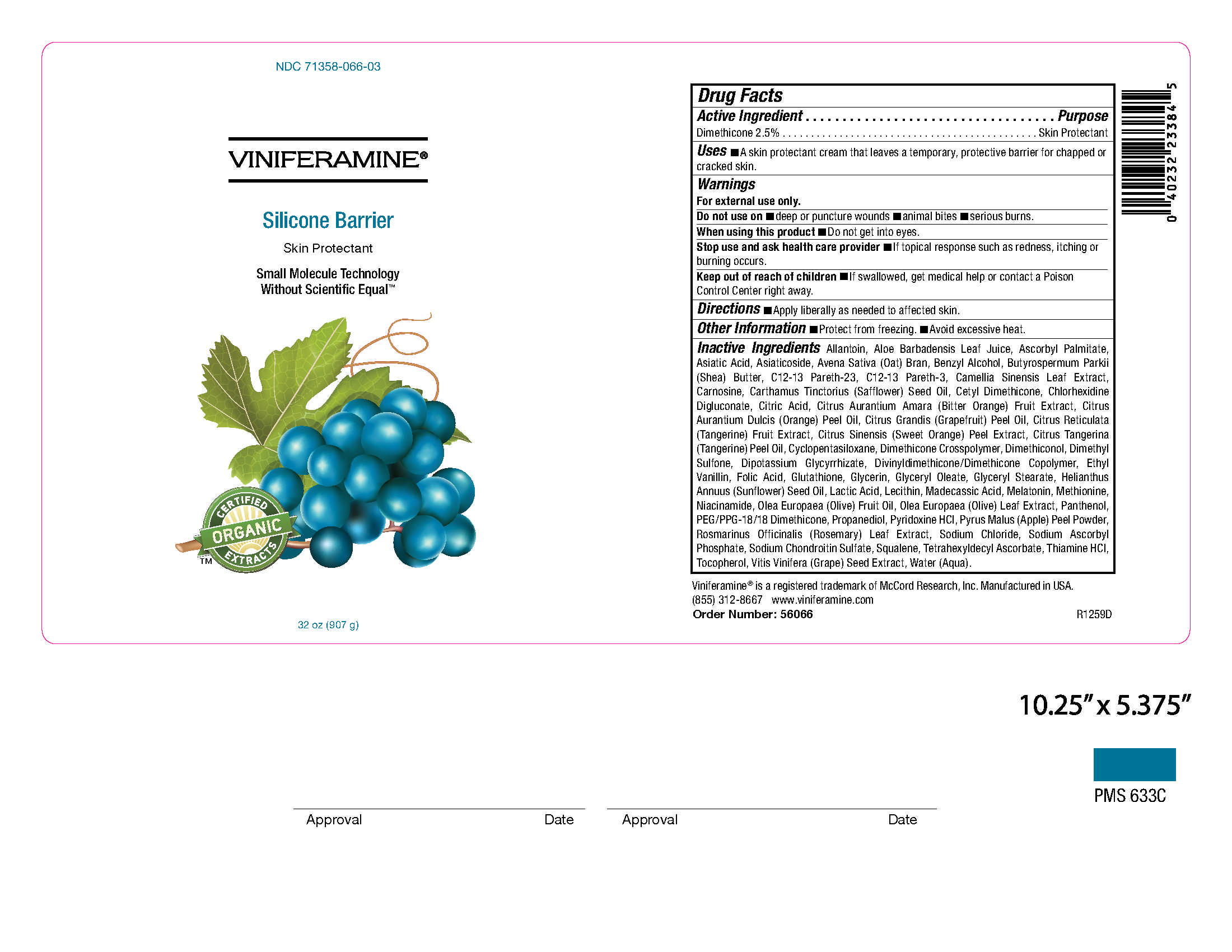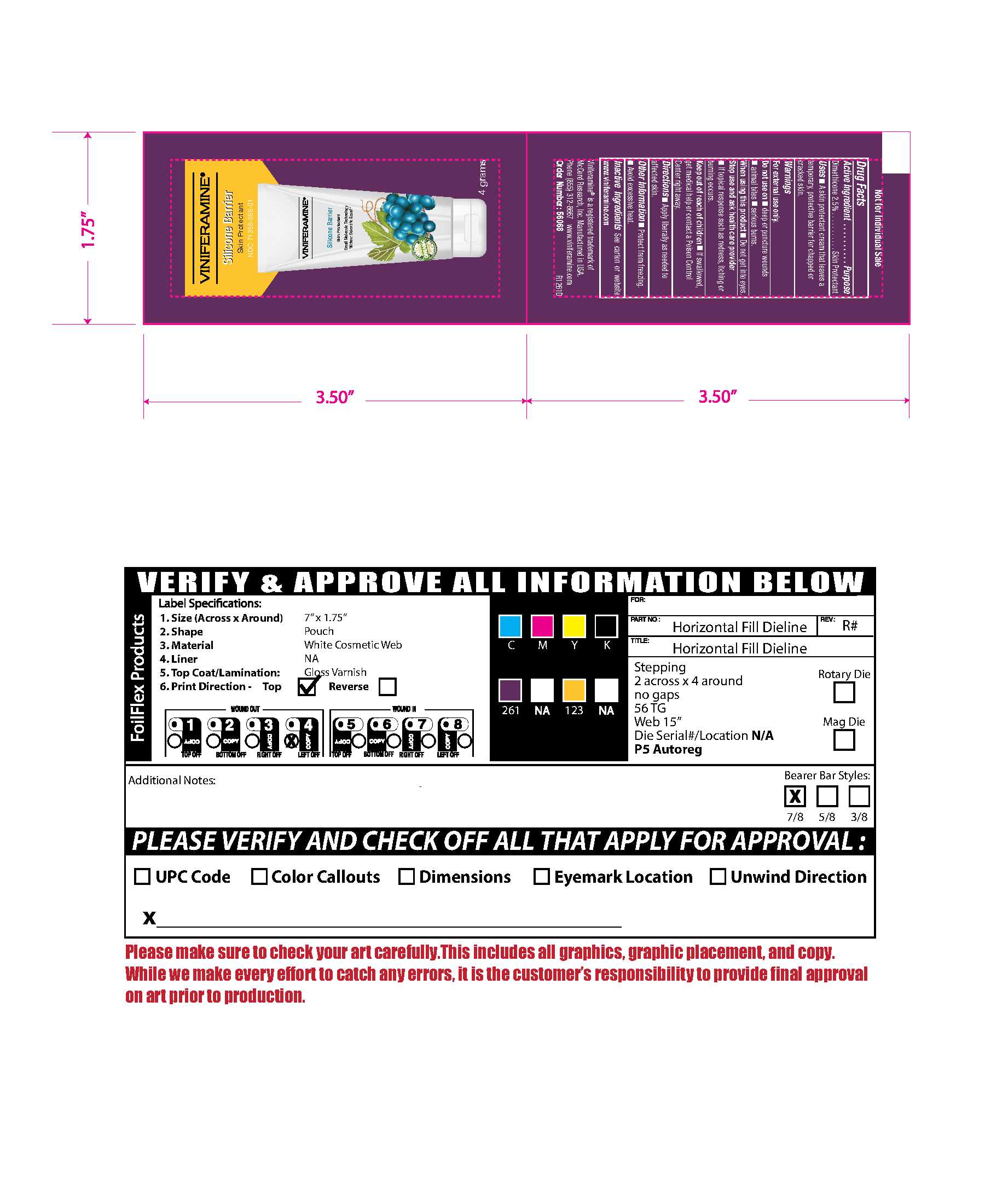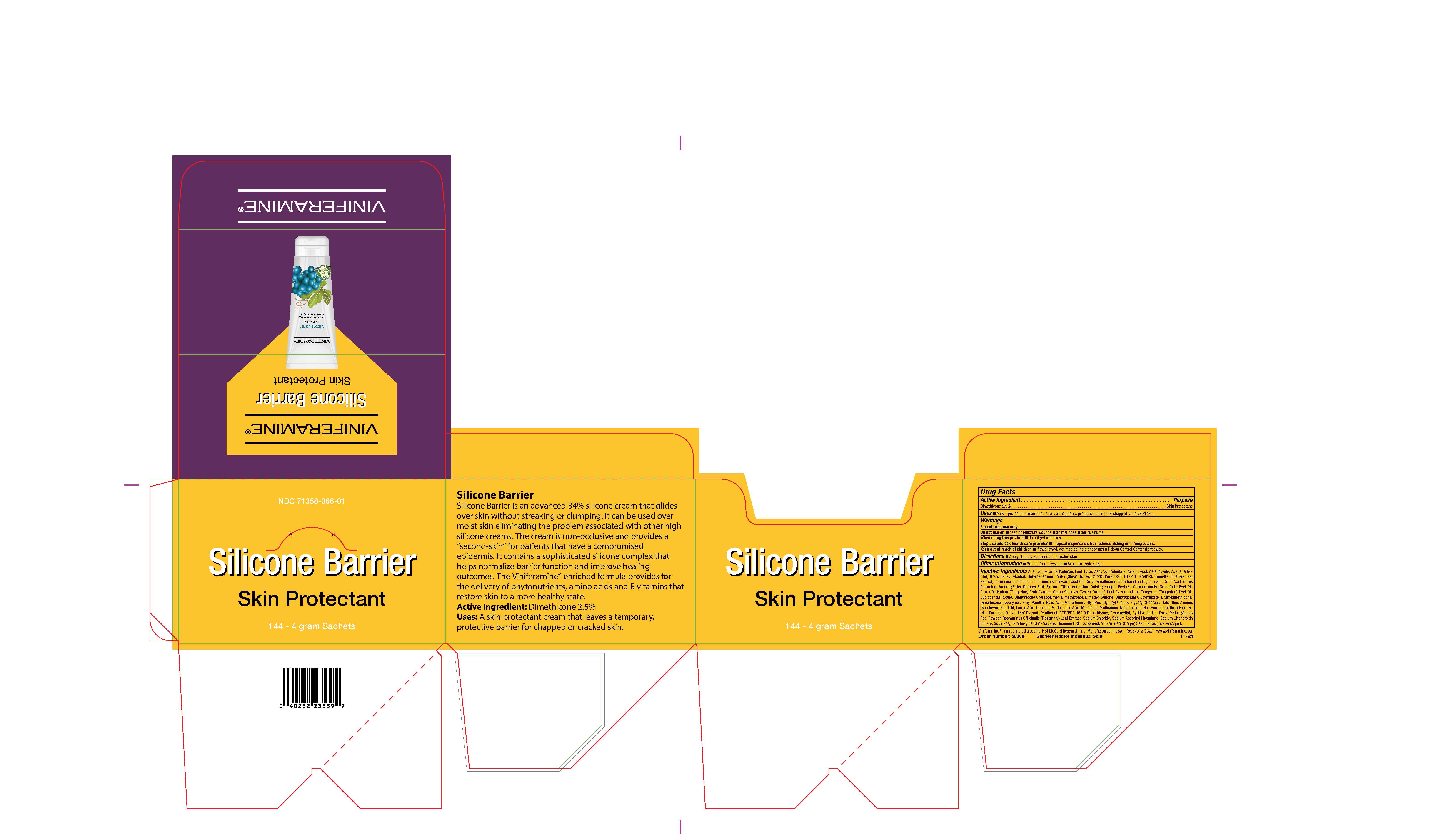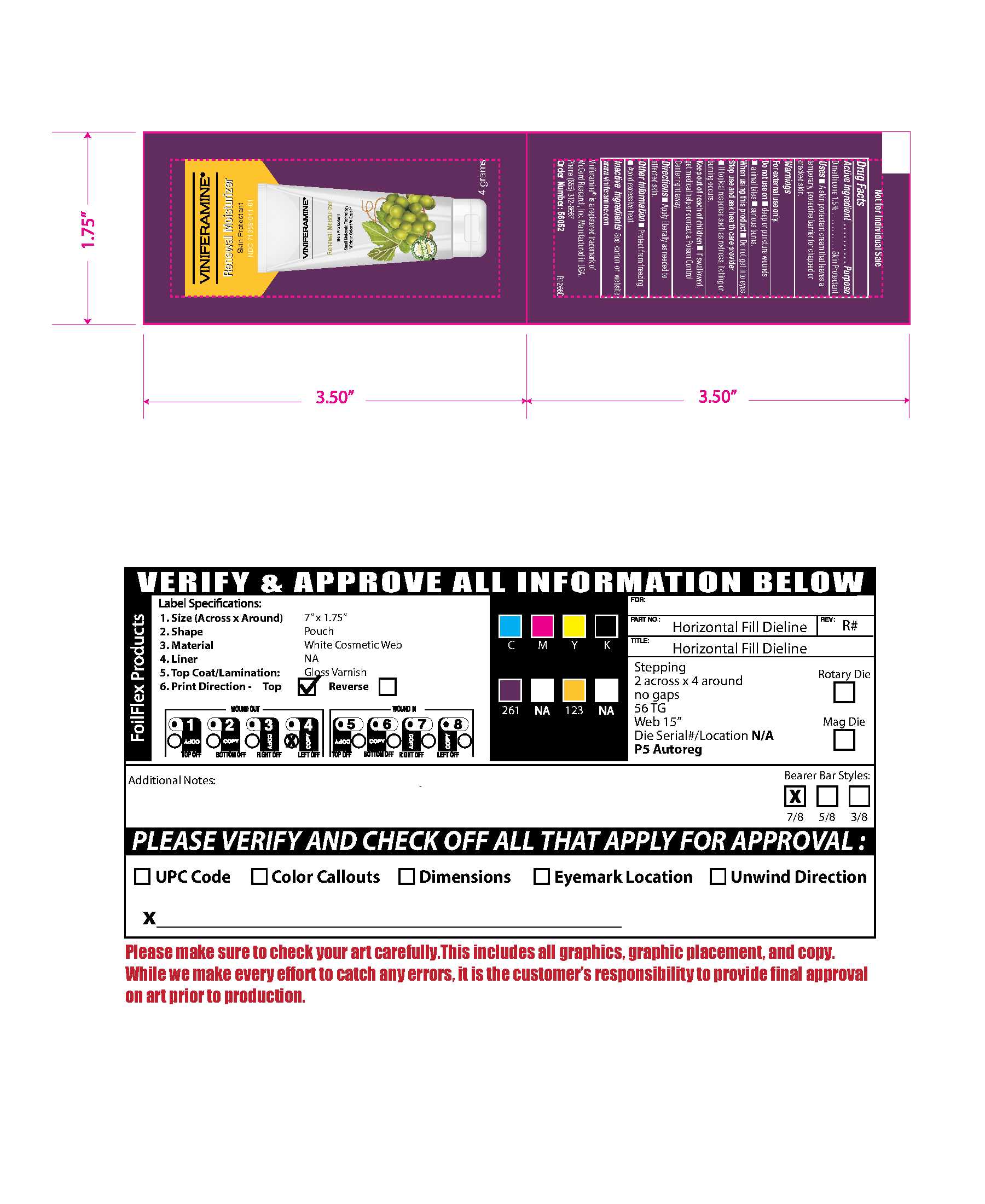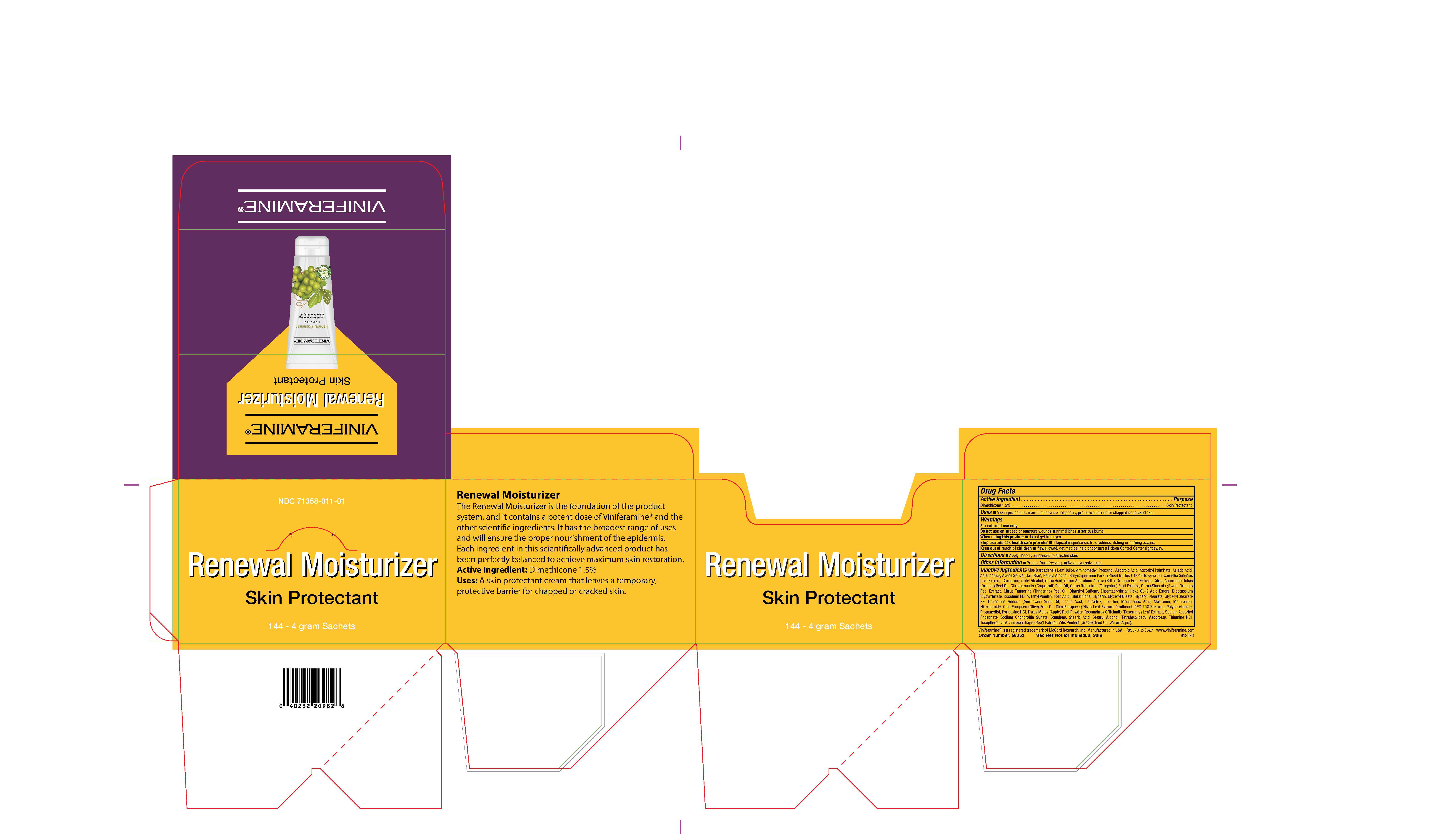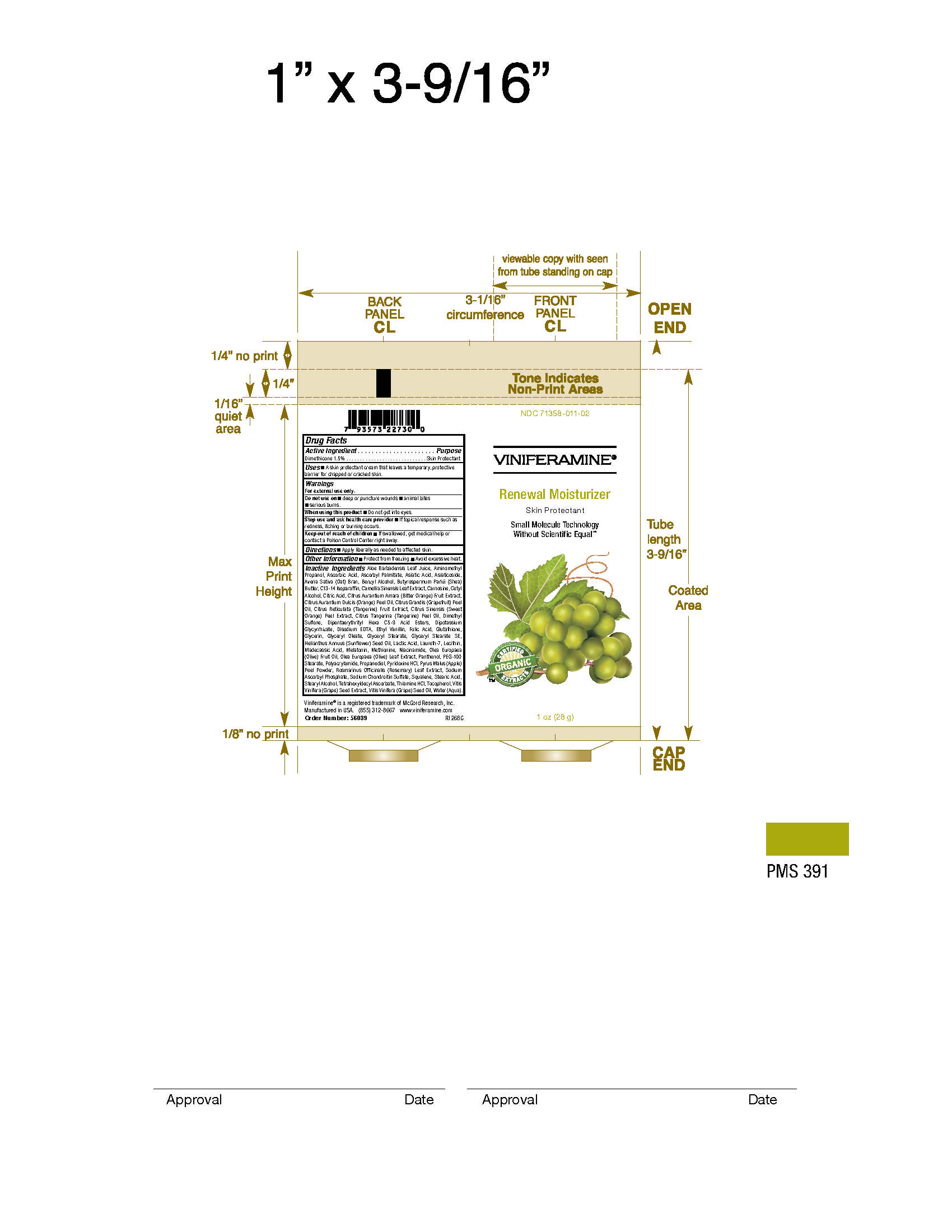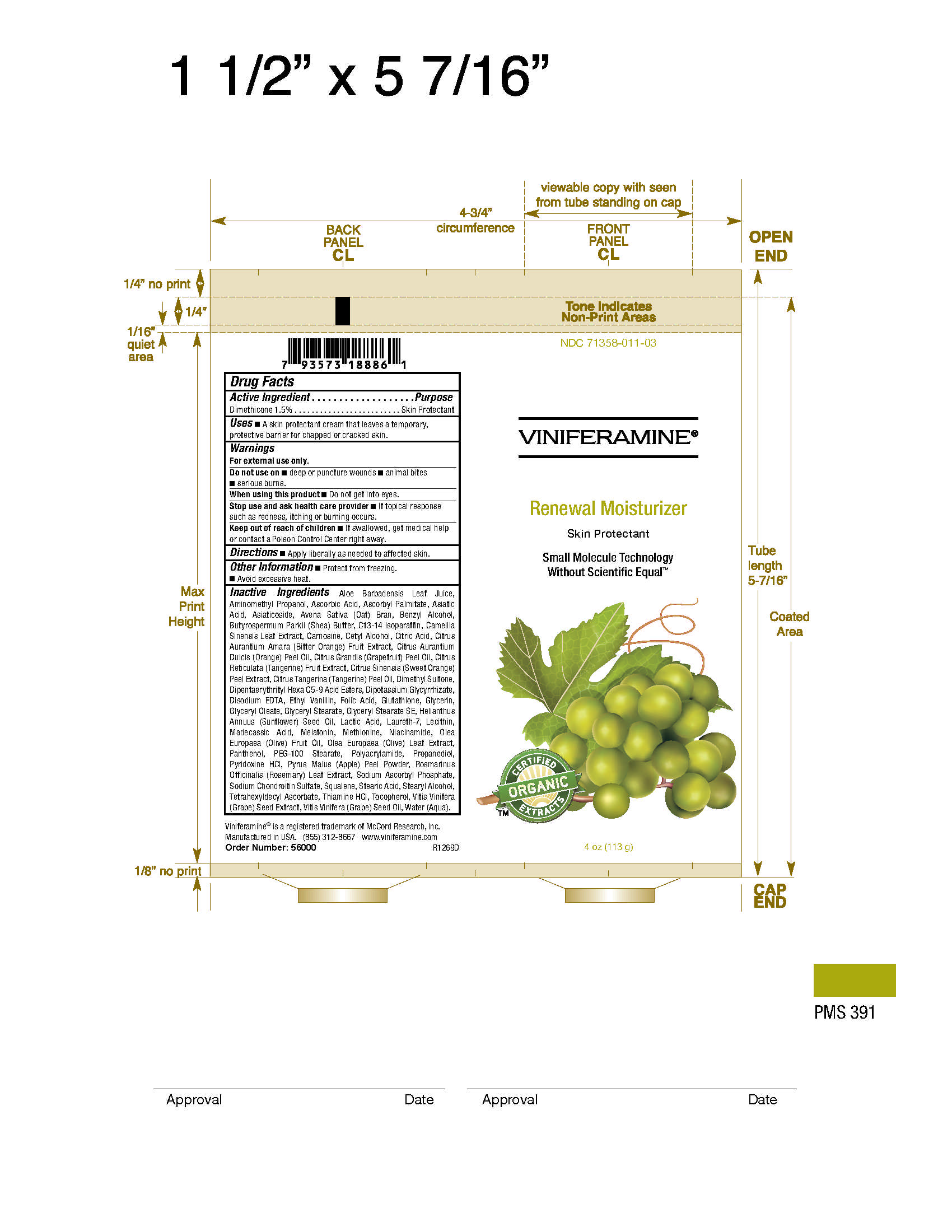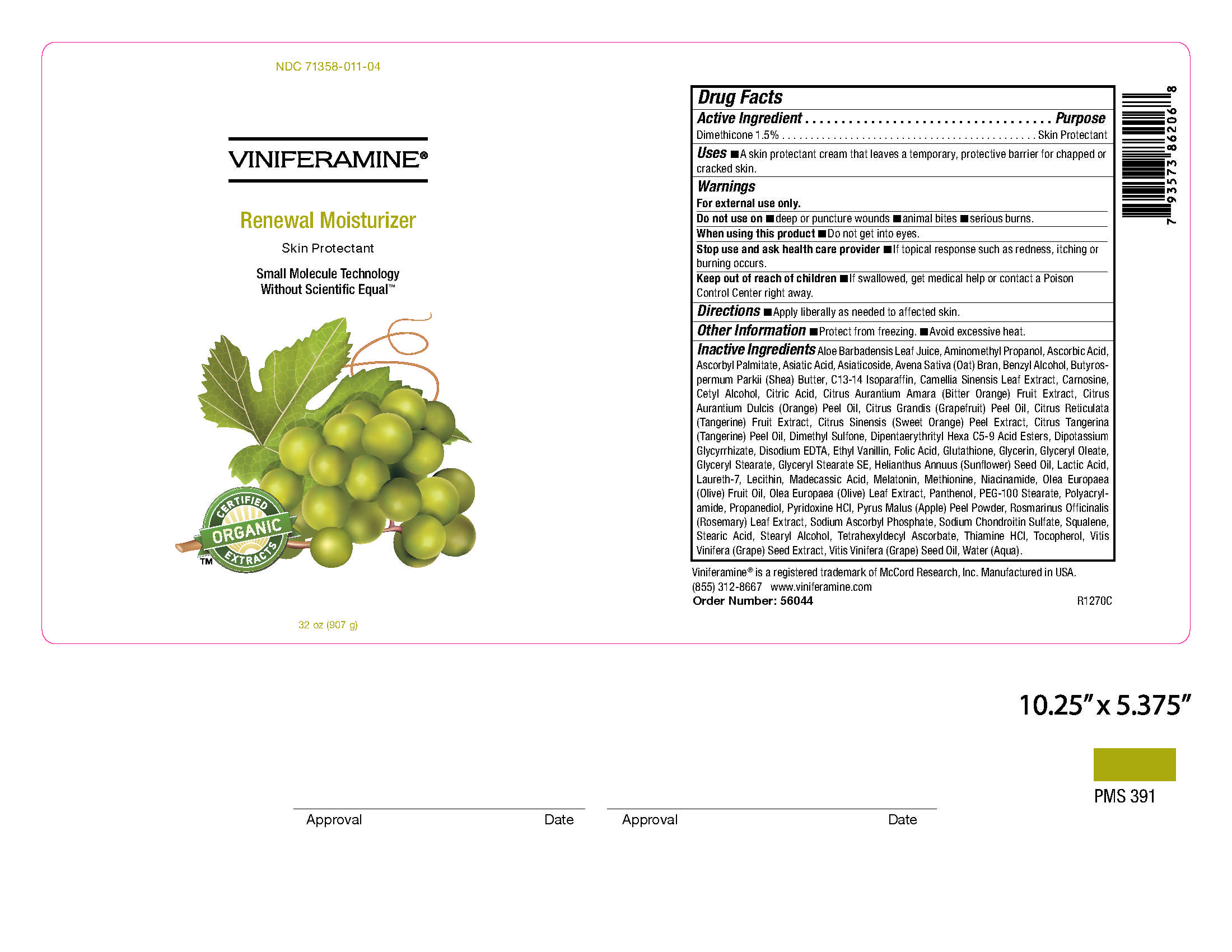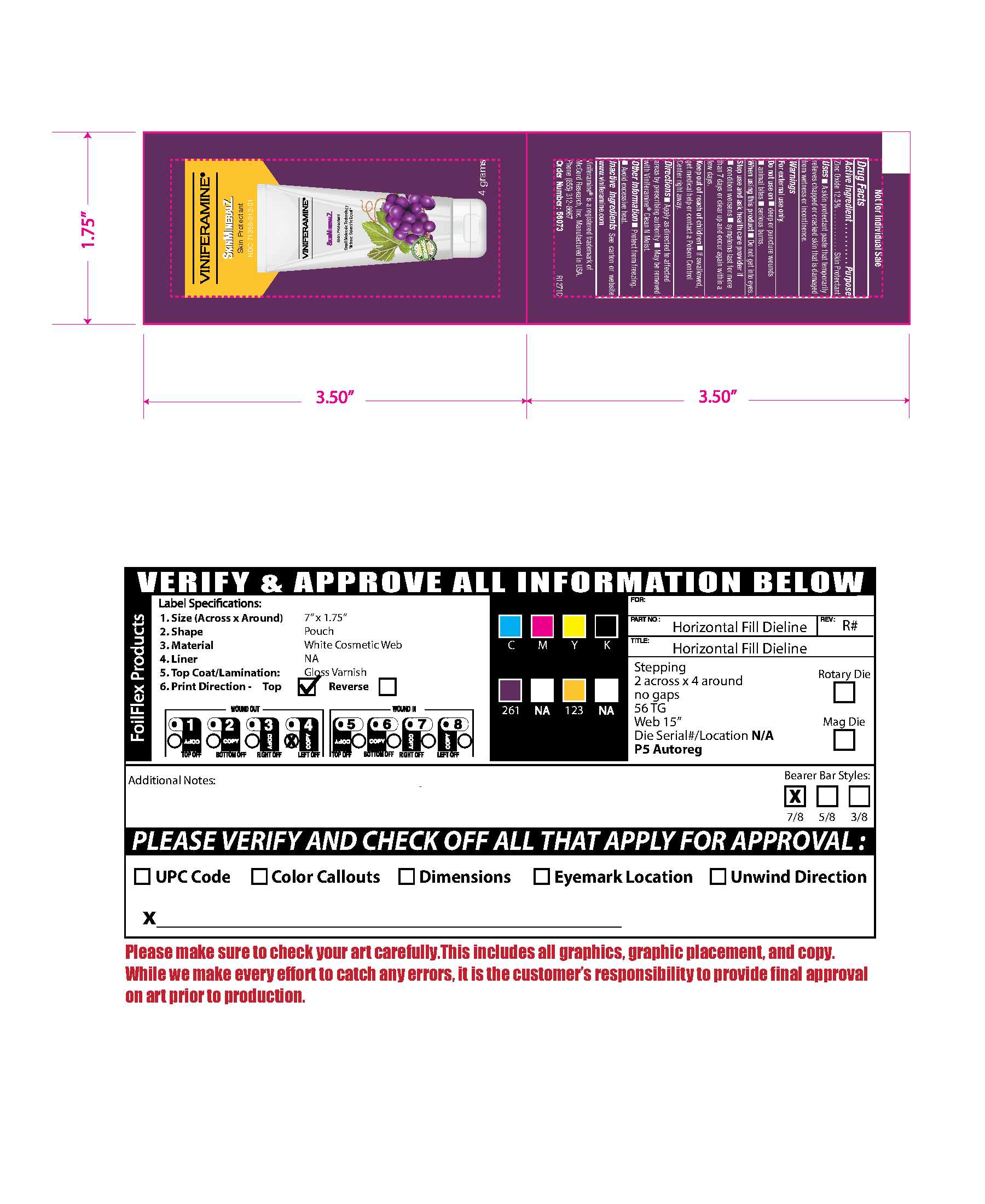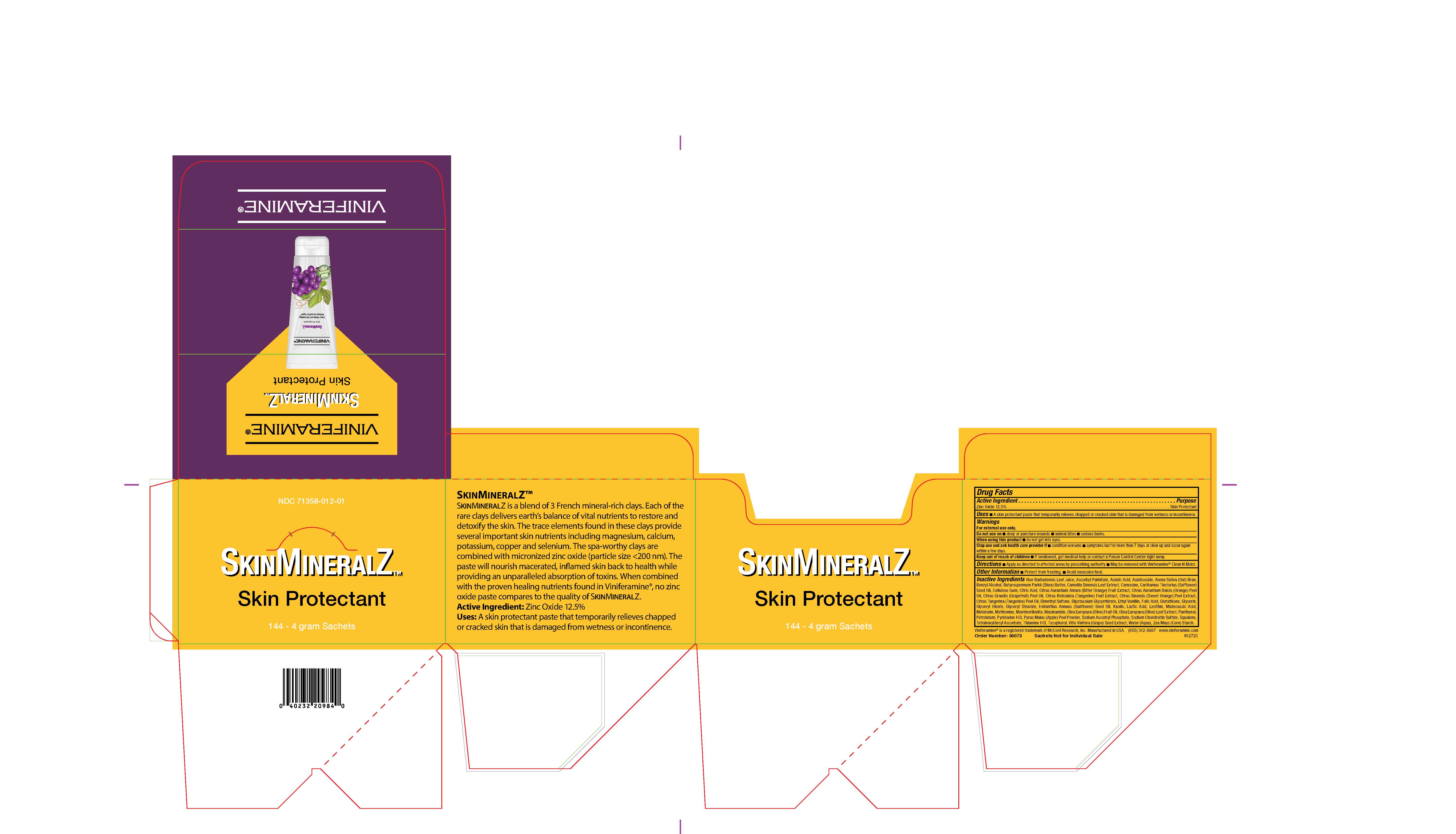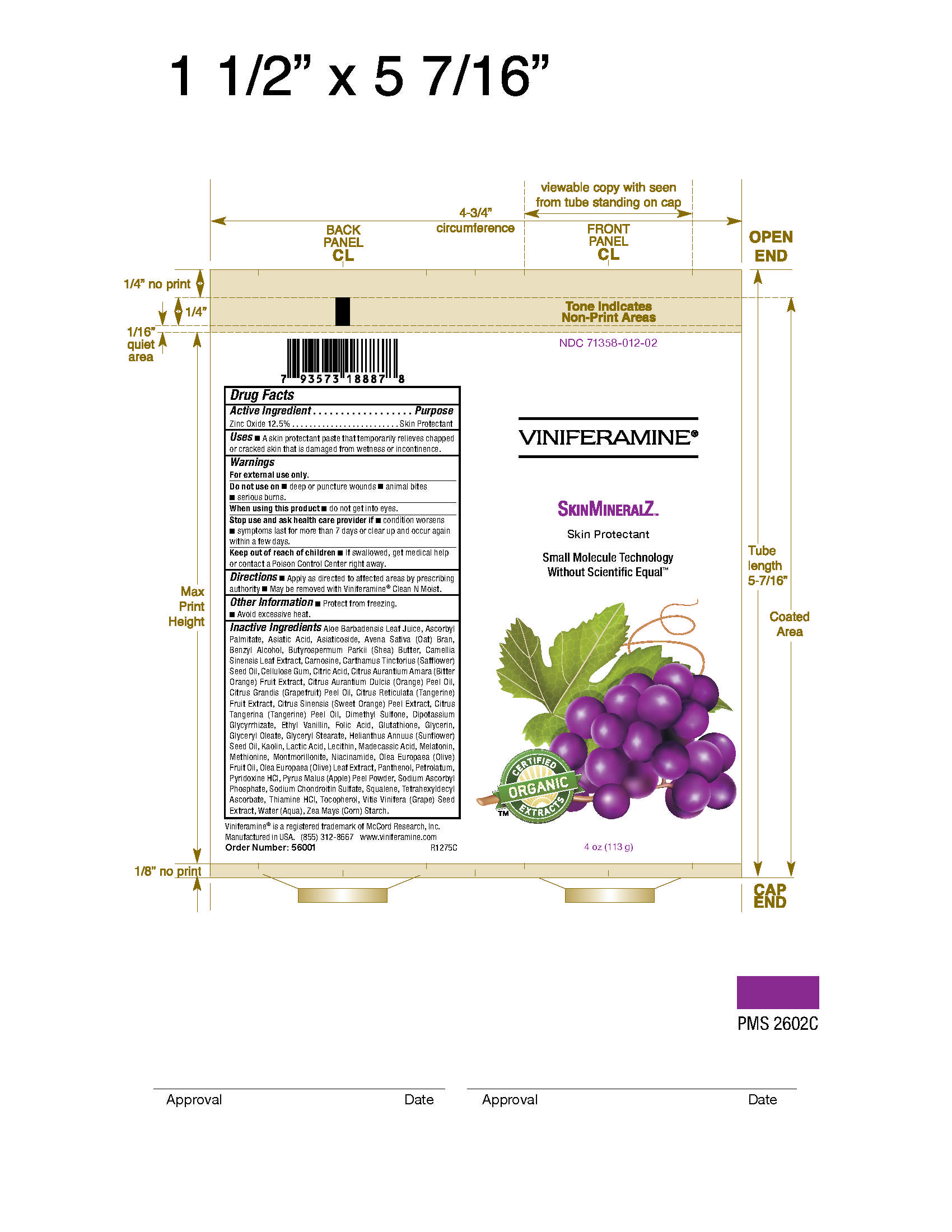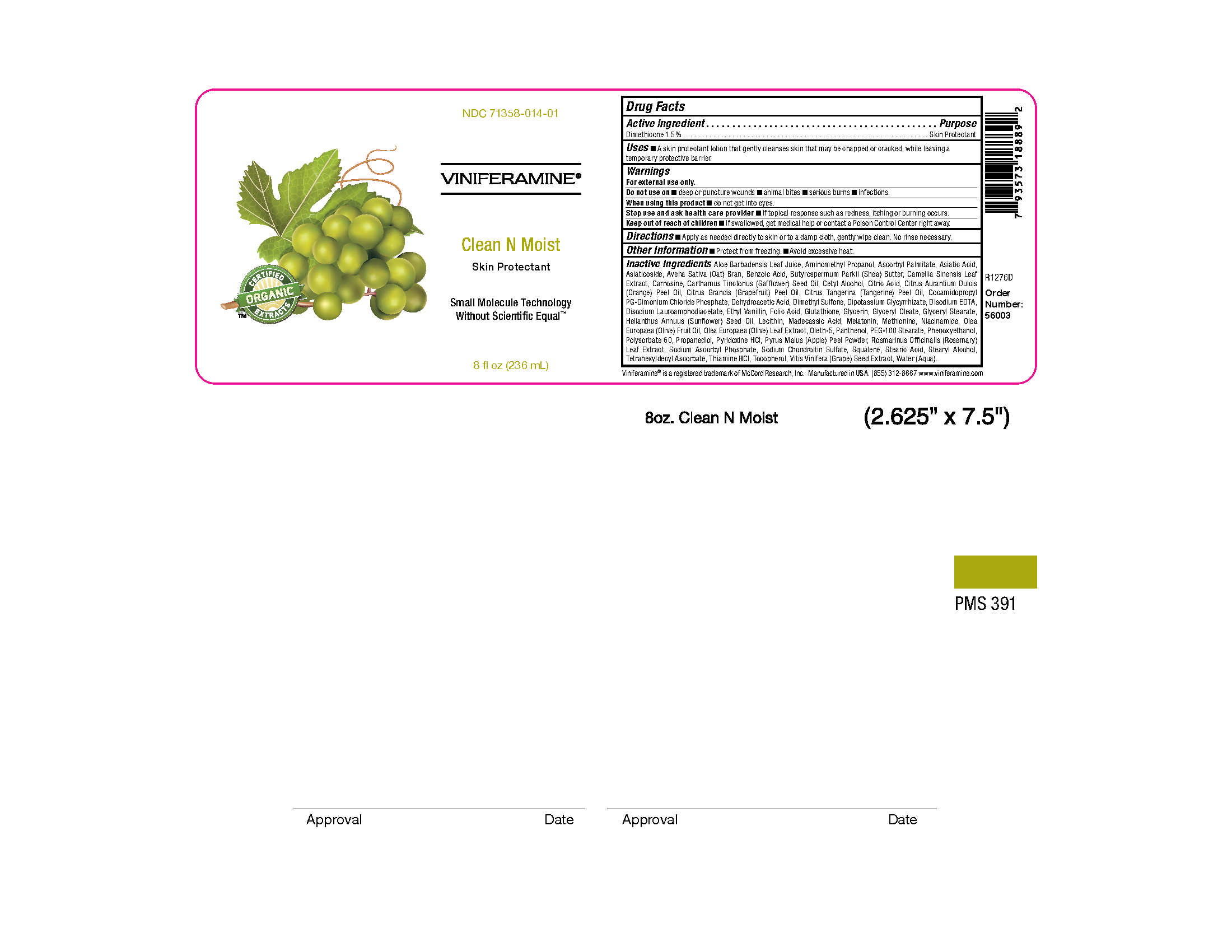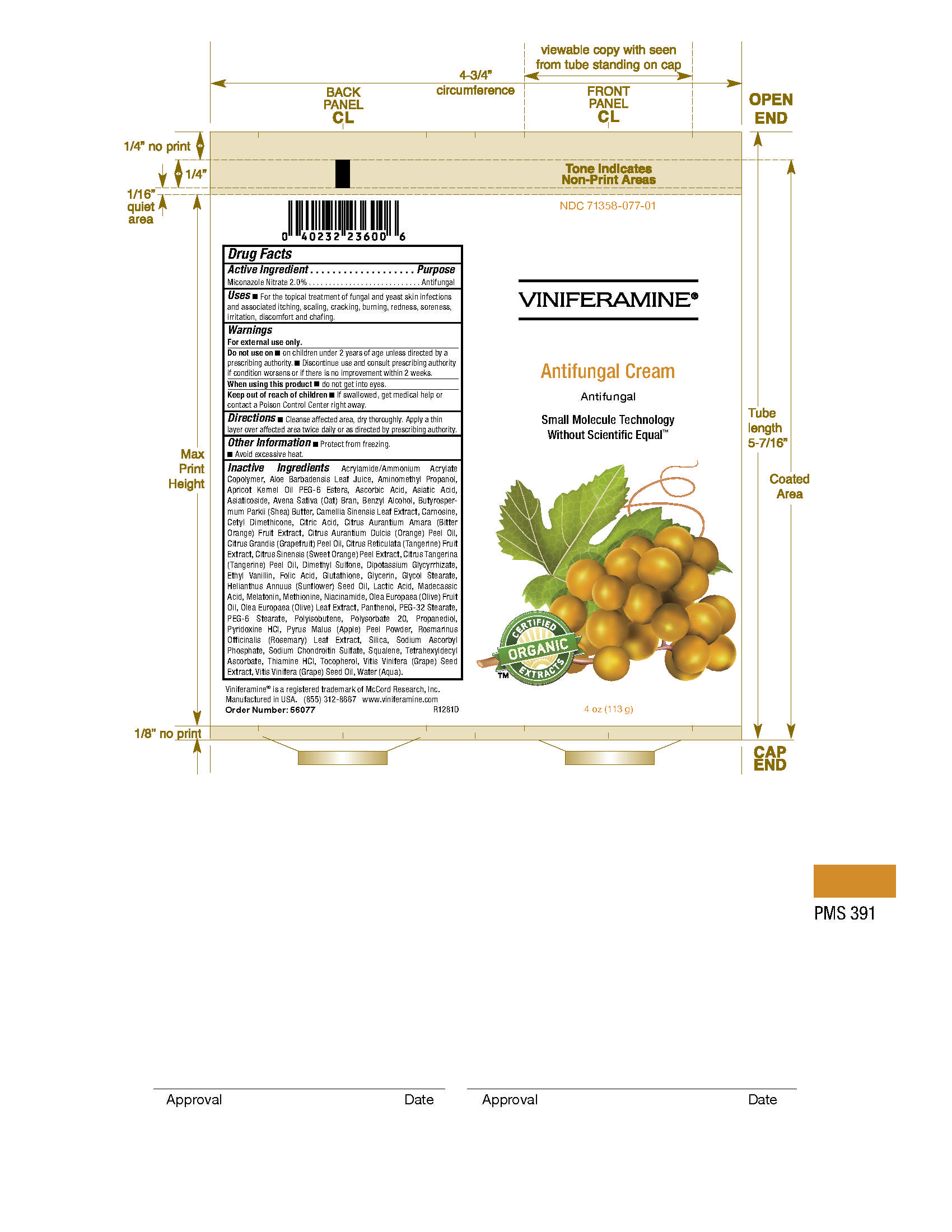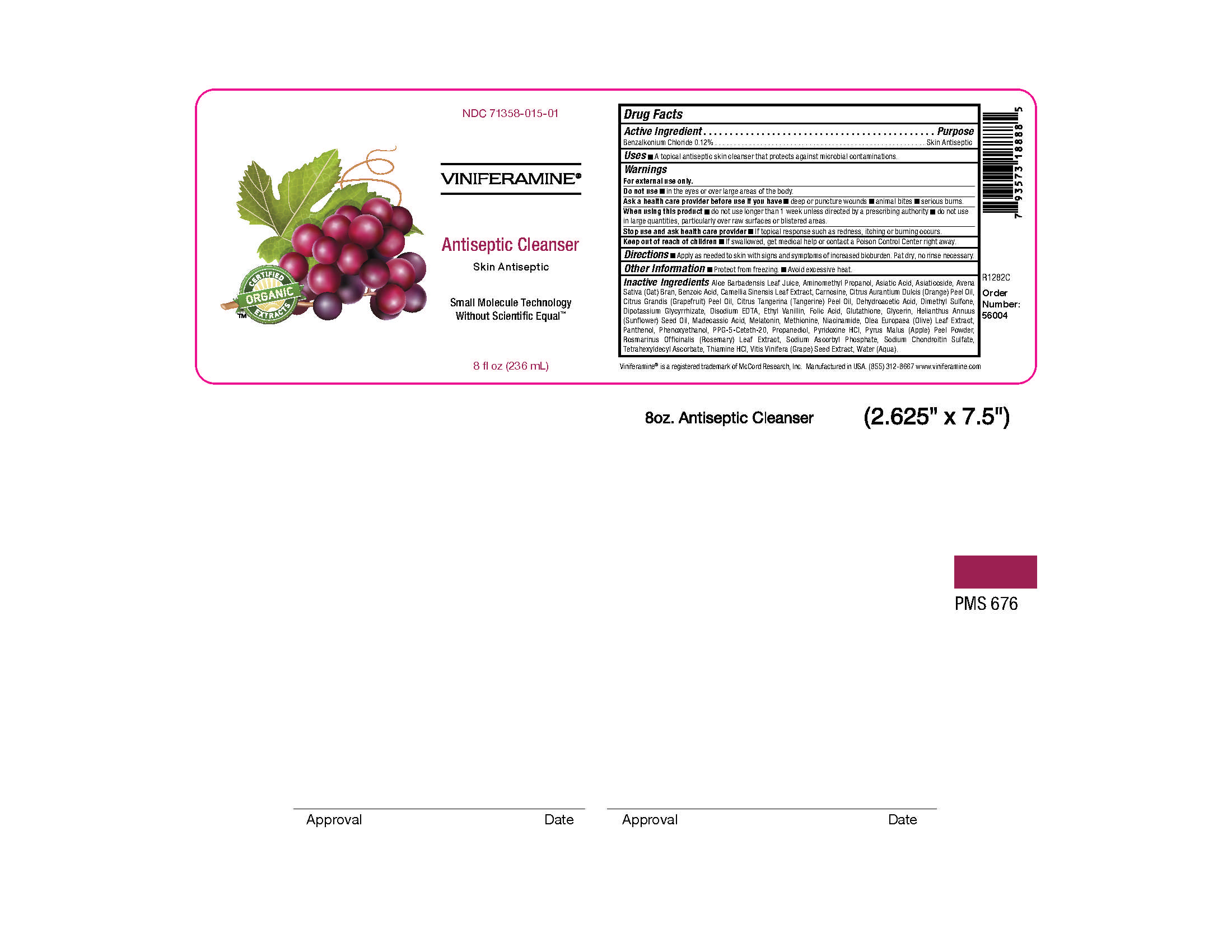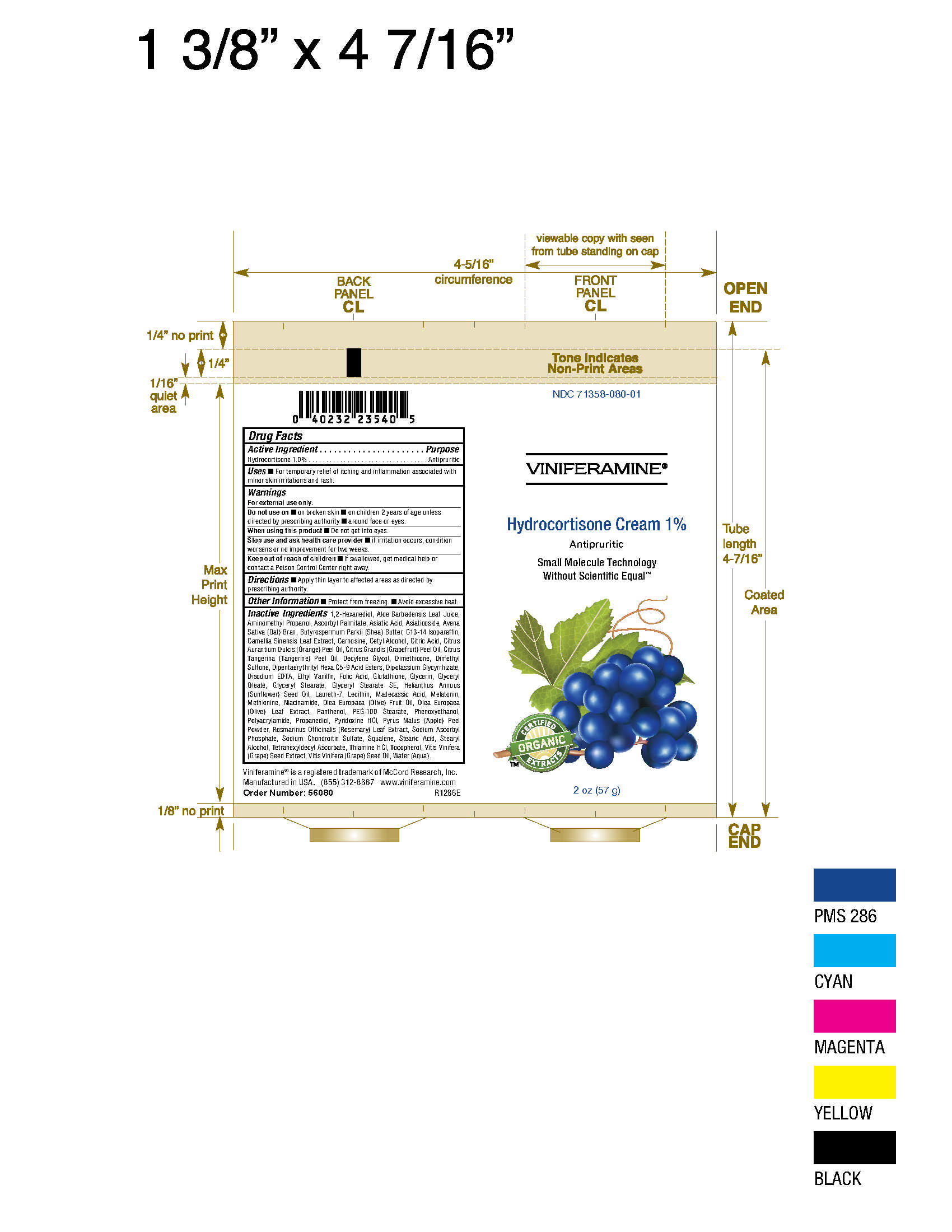 DRUG LABEL: Viniferamine Renewal Moisturizer
NDC: 71358-011 | Form: CREAM
Manufacturer: McCord Research
Category: otc | Type: HUMAN OTC DRUG LABEL
Date: 20220118

ACTIVE INGREDIENTS: DIMETHICONE 15 mg/1 g
INACTIVE INGREDIENTS: ASCORBIC ACID

Viniferamine OTC drug listings

All products

See image within Principal Display Sections for each product

All products

See image within Principal Display Sections for each product

All products

See image within Principal Display Sections for each product

All products

See image within Principal Display Sections for each product

All products

See image within Principal Display Sections for each product

All products

See image within Principal Display Sections for each product

All products

See image within Principal Display Sections for each product